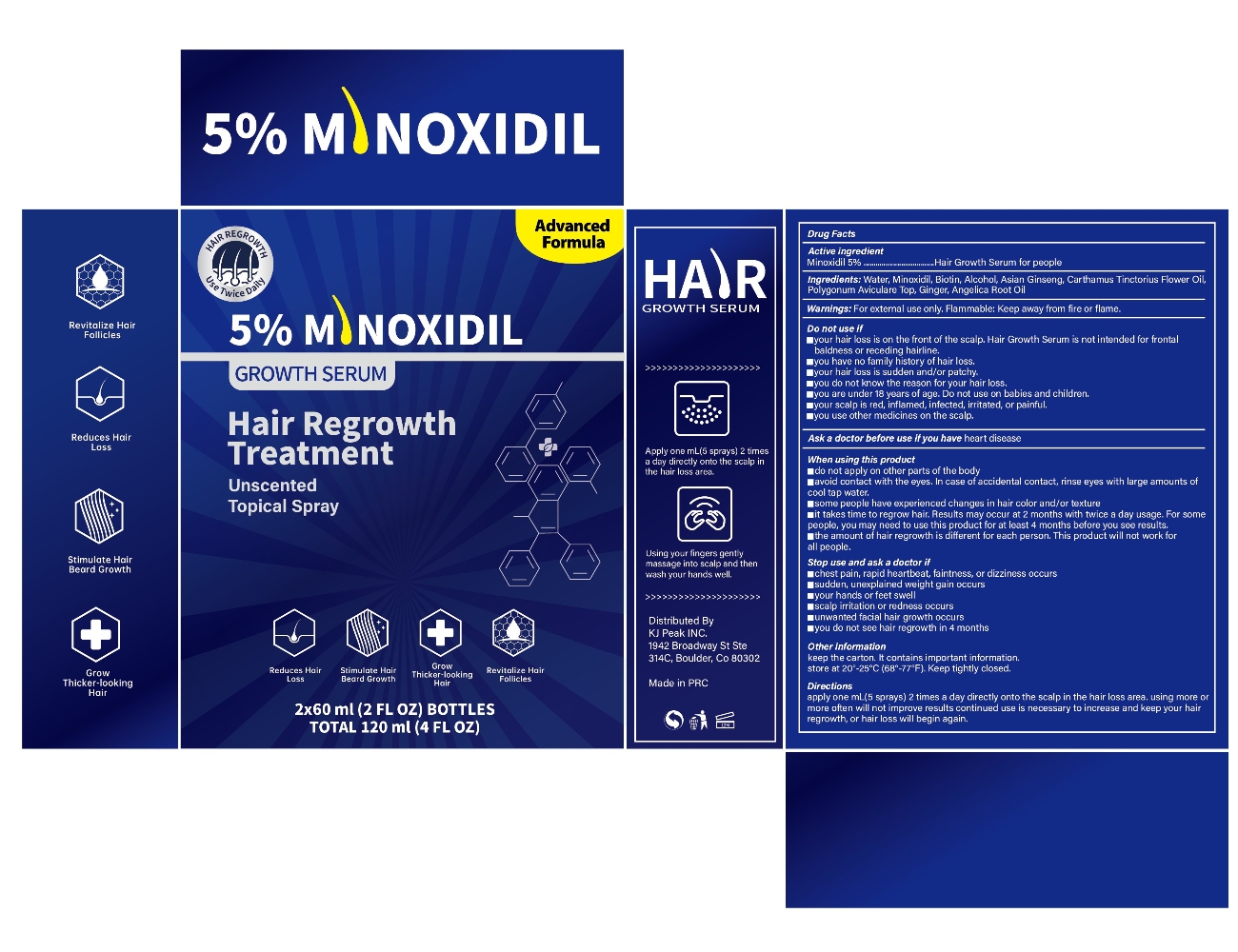 DRUG LABEL: Hair Regrowth 5% Minoxidil
NDC: 84033-007 | Form: SOLUTION
Manufacturer: Qingdao Kuajie Online Electronic Technology Co., Ltd
Category: otc | Type: HUMAN OTC DRUG LABEL
Date: 20240513

ACTIVE INGREDIENTS: MINOXIDIL 5 g/100 mL
INACTIVE INGREDIENTS: BIOTIN 3 g/100 mL; ALCOHOL 3 mL/100 mL; WATER 83 mL/100 mL; CARTHAMUS TINCTORIUS FLOWER OIL 1 g/100 mL; POLYGONUM AVICULARE TOP 1 g/100 mL; ANGELICA ROOT OIL 0.5 g/100 mL; ASIAN GINSENG 2 g/100 mL; GINGER 1 g/100 mL

ACTIVE INGREDIENT

MINOXIDIL 5%

INACTIVE INGREDIENT

BIOTIN 3g
ALCOHOL 3 mL
WATER 83 mL
CARTHAMUS TINCTORIUS FLOWER OIL 1g
POLYGONUM AVICULARE TOP 1g
ANGELICA ROOT OIL 0.5g
ASIAN GINSENG 2 g
GINGER 1g

PURPOSE

Hair Growth

HOW TO USE

Apply 1 ML(few drops)directly onto scalp on the hair loss area.
Use fingertips to massage solution into skin/hair for 2-3 minutes or use a roller to roll 4-5 times.
Allow time for hair to fully absorb Growth Oil, don't apply anything to your hair for a few hours.

WARNINGS

For external use only. For use by men only.
Flammable : Keep away from fire or flame.
Keep out of reach of children.

STOP USE AND ASK A DOCTOR IF

Chest pain, rapid heartbeat, faintness, or dizziness occurs
Sudden, unexplained weight gain occurs
Your hands or feet swell
Scalp irritation or redness occurs
Unwanted facial hair growth occurs
You do not see hair regrowth in 4 months

DO NOT USE IF

your hair loss is on the front of the scalp. 5% minoxidil topical solution is not intended for frontal baldness or receding hairline.
you have no family history of hair loss.
your hair loss is sudden and/or patchy.
you do not know the reason for your hair loss.
you are under 18 years of age. Do not use on babies and children.
your scalp is red, inflamed, infected, irritated, or painful.
you use other medicines on the scalp.
Ask a doctor before use if you have heart disease.
May be harmful if used when pregnant or breast-feeding.

WHEN USING THIS PRODUCT

Do not apply on other parts of the body.
Avoid contact with the eyes. In case of accidental contact, rinse eyes with large amounts of cool tap water.
Some people have experienced changes in hair color and/or texture.
It takes time to regrow hair. Results may occur at 2 months with twice a day usage.
For some men, you may need to use this product for at least 4 months before you see results.
The amount of hair regrowth is different for each person.
This product will not work for all men.

STORAGE

Store in a dark, cool place.
Store at controlled room temperature 59°F-77°F(15°C-25°C).
Keep out of direct sunlight.
Keep the cap on tightly when not in use.

KEEP OUT OF REACH OF CHILDREN

Flammable : Keep away from fire or flame.
Keep out of reach of children.

DOSAGE

Apply 1 ML(few drops)directly onto scalp on the hair loss area.
Use fingertips to massage solution into skin/hair for 2-3 minutes or use a roller to roll 4-5 times.
Allow time for hair to fully absorb Growth Oil, don't apply anything to your hair for a few hours.